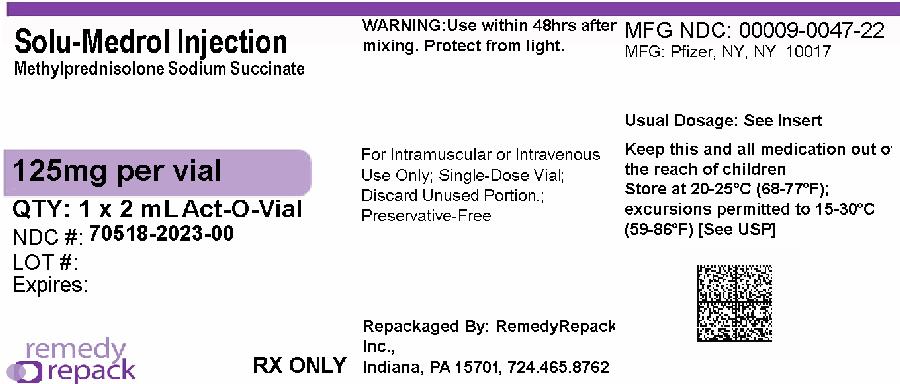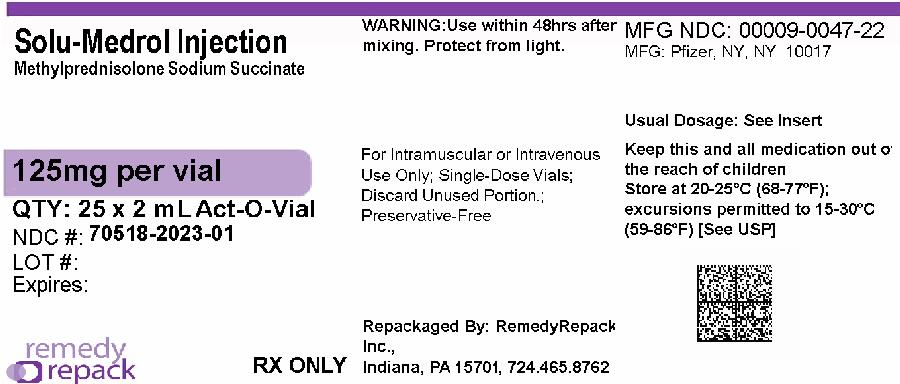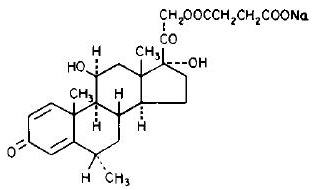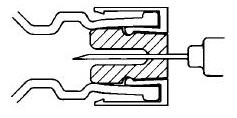 DRUG LABEL: SOLU-MEDROL
NDC: 70518-2023 | Form: INJECTION, POWDER, FOR SOLUTION
Manufacturer: REMEDYREPACK INC.
Category: prescription | Type: HUMAN PRESCRIPTION DRUG LABEL
Date: 20260130

ACTIVE INGREDIENTS: METHYLPREDNISOLONE SODIUM SUCCINATE 125 mg/2 mL
INACTIVE INGREDIENTS: SODIUM PHOSPHATE, MONOBASIC, ANHYDROUS 1.6 mg/2 mL; SODIUM PHOSPHATE, DIBASIC, UNSPECIFIED FORM 17.4 mg/2 mL

SOLU-MEDROL®(methylprednisolone sodium succinate for injection, USP)

The formulations containing benzyl alcohol should not be used in neonates.

For Intravenous or Intramuscular Administration

DESCRIPTION

SOLU-MEDROL Sterile Powder is an anti-inflammatory glucocorticoid, which contains methylprednisolone sodium succinate as the active ingredient. Methylprednisolone sodium succinate, USP, is the sodium succinate ester of methylprednisolone, and it occurs as a white, or nearly white, odorless hygroscopic, amorphous solid. It is very soluble in water and in alcohol; it is insoluble in chloroform and is very slightly soluble in acetone.

The chemical name for methylprednisolone sodium succinate is pregna-1,4-diene-3,20-dione,21-(3-carboxy-1-oxopropoxy)-11,17-dihydroxy-6-methyl-monosodium salt, (6α, 11β), and the molecular weight is 496.53. The structural formula is represented below:

Methylprednisolone sodium succinate is soluble in water; it may be administered in a small volume of diluent and is well suited for intravenous use in situations where high blood levels of methylprednisolone are required rapidly.

SOLU-MEDROL is available in preservative and preservative-free formulations:

Preservative-free Formulations

40 mg Act-O-Vial System (Single-Dose Vial)—Each mL (when mixed) contains methylprednisolone sodium succinate equivalent to 40 mg methylprednisolone; also
1.6 mg monobasic sodium phosphate anhydrous; 17.46 mg dibasic sodium phosphate dried; and 25 mg lactose hydrous.

125 mg Act-O-Vial System (Single-Dose Vial)—Each 2 mL (when mixed) contains methylprednisolone sodium succinate equivalent to 125 mg methylprednisolone; also
1.6 mg monobasic sodium phosphate anhydrous; and 17.4 mg dibasic sodium phosphate dried.

500 mg Act-O-Vial System (Single-Dose Vial)—Each 4 mL (when mixed) contains methylprednisolone sodium succinate equivalent to 500 mg methylprednisolone; also
6.4 mg monobasic sodium phosphate anhydrous; and 69.6 mg dibasic sodium phosphate dried.

1 gram Act-O-Vial System (Single-Dose Vial)—Each 8 mL (when mixed) contains methylprednisolone sodium succinate equivalent to 1 gram methylprednisolone; also
12.8 mg monobasic sodium phosphate anhydrous; and 139.2 mg dibasic sodium phosphate dried.

Formulations preserved with Benzyl Alcohol

500 mg Vial—Each 8 mL (when mixed as directed) contains methylprednisolone sodium succinate equivalent to 500 mg methylprednisolone; also 6.4 mg monobasic sodium phosphate anhydrous; 69.6 mg dibasic sodium phosphate dried.
This package does not contain diluent. Recommended diluent (Bacteriostatic water) contains benzyl alcohol as a preservative.

1 gram Vial—Each 16 mL (when mixed as directed) contains methylprednisolone sodium succinate equivalent to 1 gram methylprednisolone; also 12.8 mg monobasic sodium phosphate anhydrous; 139.2 mg dibasic sodium phosphate dried.
This package does not contain diluent. Recommended diluent (Bacteriostatic water) contains benzyl alcohol as a preservative.

2 gram Vial—Each 30.6 mL (when mixed as directed) contains methylprednisolone sodium succinate equivalent to 2 grams methylprednisolone; also 25.6 mg monobasic sodium phosphate anhydrous; 278 mg dibasic sodium phosphate dried.
This package does not contain diluent. Recommended diluent (Bacteriostatic water) contains benzyl alcohol as a preservative.

IMPORTANT— Use only the accompanying diluent
or Bacteriostatic Water For Injection with
Benzyl Alcohol when reconstituting SOLU-MEDROL.
Use within 48 hours after mixing.

When necessary, the pH of each formula was adjusted with sodium hydroxide so that the pH of the reconstituted solution is within the USP specified range of 7 to 8.

CLINICAL PHARMACOLOGY

Glucocorticoids, naturally occurring and synthetic, are adrenocortical steroids that are readily absorbed from the gastrointestinal tract.

Naturally occurring glucocorticoids (hydrocortisone and cortisone), which also have salt-retaining properties, are used as replacement therapy in adrenocortical deficiency states. Their synthetic analogs are primarily used for their potent anti-inflammatory effects in disorders of many organ systems.

Glucocorticoids cause profound and varied metabolic effects. In addition, they modify the body's immune responses to diverse stimuli.

Methylprednisolone is a potent anti-inflammatory steroid with greater anti-inflammatory potency than prednisolone and even less tendency than prednisolone to induce sodium and water retention.

Methylprednisolone sodium succinate has the same metabolic and anti-inflammatory actions as methylprednisolone. When given parenterally and in equimolar quantities, the two compounds are equivalent in biologic activity. Following the intravenous injection of methylprednisolone sodium succinate, demonstrable effects are evident within one hour and persist for a variable period. Excretion of the administered dose is nearly complete within 12 hours. Thus, if constantly high blood levels are required, injections should be made every 4 to 6 hours. This preparation is also rapidly absorbed when administered intramuscularly and is excreted in a pattern similar to that observed after intravenous injection.

INDICATIONS AND USAGE

When oral therapy is not feasible, and the strength, dosage form, and route of administration of the drug reasonably lend the preparation to the treatment of the condition, the intravenous or intramuscular useof SOLU-MEDROL Sterile Powder is indicated as follows:

Allergic states: Control of severe or incapacitating allergic conditions intractable to adequate trials of conventional treatment in asthma, atopic dermatitis, contact dermatitis, drug hypersensitivity reactions, serum sickness, transfusion reactions.

Dermatologic diseases: Bullous dermatitis herpetiformis, exfoliative erythroderma, mycosis fungoides, pemphigus, severe erythema multiforme (Stevens-Johnson syndrome).

Endocrine disorders: Primary or secondary adrenocortical insufficiency (hydrocortisone or cortisone is the drug of choice; synthetic analogs may be used in conjunction with mineralocorticoids where applicable; in infancy, mineralocorticoid supplementation is of particular importance), congenital adrenal hyperplasia, hypercalcemia associated with cancer, nonsuppurative thyroiditis.

Gastrointestinal diseases: To tide the patient over a critical period of the disease in regional enteritis (systemic therapy) and ulcerative colitis.

Hematologic disorders: Acquired (autoimmune) hemolytic anemia, congenital (erythroid) hypoplastic anemia (Diamond-Blackfan anemia), idiopathic thrombocytopenic purpura in adults (intravenous administration only; intramuscular administration is contraindicated), pure red cell aplasia, selected cases of secondary thrombocytopenia.

Miscellaneous: Trichinosis with neurologic or myocardial involvement, tuberculous meningitis with subarachnoid block or impending block when used concurrently with appropriate antituberculous chemotherapy.

Neoplastic diseases: For the palliative management of leukemias and lymphomas.

Nervous System: Acute exacerbations of multiple sclerosis; cerebral edema associated with primary or metastatic brain tumor, or craniotomy.

Ophthalmic diseases:Sympathetic ophthalmia, uveitis and ocular inflammatory conditions unresponsive to topical corticosteroids.

Renal diseases:To induce diuresis or remission of proteinuria in idiopathic nephrotic syndrome or that due to lupus erythematosus.

Respiratory diseases:Berylliosis, fulminating or disseminated pulmonary tuberculosis when used concurrently with appropriate antituberculous chemotherapy, idiopathic eosinophilic pneumonias, symptomatic sarcoidosis.

Rheumatic disorders: As adjunctive therapy for short-term administration (to tide the patient over an acute episode or exacerbation) in acute gouty arthritis; acute rheumatic carditis; ankylosing spondylitis; psoriatic arthritis; rheumatoid arthritis, including juvenile rheumatoid arthritis (selected cases may require low-dose maintenance therapy). For the treatment of dermatomyositis, temporal arteritis, polymyositis, and systemic lupus erythematosus.

CONTRAINDICATIONS

SOLU-MEDROL Sterile Powder is contraindicated:

- in systemic fungal infections and patients with known hypersensitivity to the product and its constituents. The SOLU-MEDROL 40 mg presentation includes lactose monohydrate produced from cow's milk. This presentation is therefore contraindicated in patients with a known or suspected hypersensitivity to cow's milk or its components or other dairy products because it may contain trace amounts of milk ingredients.
- for intrathecal administration. Reports of severe medical events have been associated with this route of administration.

Intramuscular corticosteroid preparations are contraindicated for idiopathic thrombocytopenic purpura.

Additional contraindication for the use of SOLU-MEDROL Sterile Powder preserved with benzyl alcohol:

Formulations preserved with benzyl alcohol are contraindicated for use in premature infants (see WARNINGSand PRECAUTIONS, Pediatric Use).

WARNINGS

Serious Neurologic Adverse Reactions with Epidural Administration

Serious neurologic events, some resulting in death, have been reported with epidural injection of corticosteroids. Specific events reported include, but are not limited to, spinal cord infarction, paraplegia, quadriplegia, cortical blindness, and stroke. These serious neurologic events have been reported with and without use of fluoroscopy. The safety and effectiveness of epidural administration of corticosteroids have not been established, and corticosteroids are not approved for this use.

General

Formulations with preservative (see DESCRIPTION) contain benzyl alcohol, which is potentially toxic when administered locally to neural tissue. Exposure to excessive amounts of benzyl alcohol has been associated with toxicity (hypotension, metabolic acidosis), particularly in neonates, and an increased incidence of kernicterus, particularly in small preterm infants. There have been rare reports of deaths, primarily in preterm infants, associated with exposure to excessive amounts of benzyl alcohol. The amount of benzyl alcohol from medications is usually considered negligible compared to that received in flush solutions containing benzyl alcohol. Administration of high dosages of medications containing this preservative must take into account the total amount of benzyl alcohol administered. The amount of benzyl alcohol at which toxicity may occur is not known. If the patient requires more than the recommended dosages or other medications containing this preservative, the practitioner must consider the daily metabolic load of benzyl alcohol from these combined sources (see PRECAUTIONS, Pediatric Use).

Injection of SOLU-MEDROL may result in dermal and/or subdermal changes forming depressions in the skin at the injection site. In order to minimize the incidence of dermal and subdermal atrophy, care must be exercised not to exceed recommended doses in injections. Injection into the deltoid muscle should be avoided because of a high incidence of subcutaneous atrophy.

Rare instances of anaphylactoid reactions have occurred in patients receiving corticosteroid therapy (see ADVERSE REACTIONS).

In patients receiving the 40 mg presentation of SOLU-MEDROL during the treatment for acute allergic conditions and where these symptoms worsen or any new allergic symptoms occur, consideration should be given to the potential for hypersensitivity reactions to cow's milk ingredients (see CONTRAINDICATIONS). If appropriate, administration of SOLU-MEDROL should be stopped, and the patient's condition should be treated accordingly. Alternative treatments, including the use of corticosteroid formulations that do not contain ingredients produced from cow's milk, should be considered for acute allergy management, where appropriate.

Increased dosage of rapidly acting corticosteroids is indicated in patients on corticosteroid therapy who are subjected to any unusual stress before, during, and after the stressful situation.

Results from one multicenter, randomized, placebo-controlled study with methylprednisolone hemisuccinate, an intravenous corticosteroid, showed an increase in early (at 2 weeks) and late (at 6 months) mortality in patients with cranial trauma who were determined not to have other clear indications for corticosteroid treatment. High doses of systemic corticosteroids, including SOLU-MEDROL, should not be used for the treatment of traumatic brain injury.

Cardio-renal

Average and large doses of corticosteroids can cause elevation of blood pressure, salt and water retention, and increased excretion of potassium. These effects are less likely to occur with the synthetic derivatives except when used in large doses. Dietary salt restriction and potassium supplementation may be necessary. All corticosteroids increase calcium excretion.

Literature reports suggest an apparent association between the use of corticosteroids and left ventricular free wall rupture after a recent myocardial infarction; therefore, therapy with corticosteroids should be used with great caution in these patients.

There have been cases reported in which concomitant use of amphotericin B and hydrocortisone was followed by cardiac enlargement and congestive heart failure (see CONTRAINDICATIONSand PRECAUTIONS, Drug Interactions, Amphotericin B injection and potassium-depleting agents).

Endocrine

Hypothalamic-pituitary adrenal (HPA) axis suppression, Cushing's syndrome, and hyperglycemia. Monitor patients for these conditions with chronic use.

Corticosteroids can produce reversible HPA axis suppression with the potential for glucocorticosteroid insufficiency after withdrawal of treatment. Drug induced secondary adrenocortical insufficiency may be minimized by gradual reduction of dosage. This type of relative insufficiency may persist for months after discontinuation of therapy; therefore, in any situation of stress occurring during that period, hormone therapy should be reinstituted.

Immunosuppression and Increased Risk of Infection

Corticosteroids, including SOLU-MEDROL, suppress the immune system and increase the risk of infection with any pathogen, including viral, bacterial, fungal, protozoan, or helminthic pathogens. Corticosteroids can:

- Reduce resistance to new infections
- Exacerbate existing infections
- Increase the risk of disseminated infections
- Increase the risk of reactivation or exacerbation of latent infections
- Mask some signs of infection

Corticosteroid-associated infections can be mild but can be severe and at times fatal. The rate of infectious complications increases with increasing corticosteroid dosages.

A study has failed to establish the efficacy of methylprednisolone sodium succinate in the treatment of sepsis syndrome and septic shock. The study also suggests that treatment of these conditions with methylprednisolone sodium succinate may increase the risk of mortality in certain patients (i.e., patients with elevated serum creatinine levels or patients who develop secondary infections after methylprednisolone sodium succinate).

Monitor for the development of infection and consider SOLU-MEDROL withdrawal or dosage reduction as needed.

Tuberculosis

If SOLU-MEDROL is used to treat a condition in patients with latent tuberculosis or tuberculin reactivity, reactivation of the disease may occur. Closely monitor such patients for reactivation. During prolonged SOLU-MEDROL therapy, patients with latent tuberculosis or tuberculin reactivity should receive chemoprophylaxis.

Varicella Zoster and Measles Viral Infections

Varicella and measles can have a serious or even fatal course in non-immune patients taking corticosteroids, including SOLU-MEDROL. In corticosteroid-treated patients who have not had these diseases or are non-immune, particular care should be taken to avoid exposure to varicella and measles:

- If a SOLU-MEDROL-treated patient is exposed to varicella, prophylaxis with varicella zoster immune globulin (VZIG) may be indicated. If varicella develops, treatment with antiviral agents may be considered.
- If a SOLU-MEDROL-treated patient is exposed to measles, prophylaxis with immunoglobulin (IG) may be indicated.

Hepatitis B virus reactivation can occur in patients who are hepatitis B carriers treated with immunosuppressive dosages of corticosteroids, including SOLU-MEDROL. Reactivation can also occur infrequently in corticosteroid-treated patients who appear to have resolved hepatitis B infection.

Screen patients for hepatitis B infection before initiating immunosuppressive (e.g., prolonged) treatment with SOLU-MEDROL. For patients who show evidence of hepatitis B infection, recommend consultation with physicians with expertise in managing hepatitis B regarding monitoring and consideration for hepatitis B antiviral therapy.

Fungal Infections

Corticosteroids, including SOLU-MEDROL, may exacerbate systemic fungal infections; therefore, avoid SOLU-MEDROL use in the presence of such infections unless SOLU-MEDROL is needed to control drug reactions. For patients on chronic SOLU-MEDROL therapy who develop systemic fungal infections, SOLU-MEDROL withdrawal or dosage reduction is recommended.

Amebiasis

Corticosteroids, including SOLU-MEDROL, may activate latent amebiasis. Therefore, it is recommended that latent amebiasis or active amebiasis be ruled out before initiating SOLU-MEDROL in patients who have spent time in the tropics or patients with unexplained diarrhea.

Strongyloides Infestation

Corticosteroids, including SOLU-MEDROL, should be used with great care in patients with known or suspected Strongyloides (threadworm) infestation. In such patients, corticosteroid-induced immunosuppression may lead to Strongyloides hyperinfection and dissemination with widespread larval migration, often accompanied by severe enterocolitis and potentially fatal gram-negative septicemia.

Cerebral Malaria

Avoid corticosteroids, including SOLU-MEDROL, in patients with cerebral malaria.

Drug-Induced Liver Injury

Rarely, high doses of cyclically pulsed intravenous methylprednisolone (usually for the treatment of exacerbations of multiple sclerosis at doses of 1 gram/day) can induce a toxic form of acute hepatitis. The time to onset of this form of steroid-induced liver injury can be several weeks or longer. Resolution has been observed after discontinuation of treatment. However, serious liver injury can occur, sometimes resulting in acute liver failure and death. Discontinue intravenous methylprednisolone if toxic hepatitis occurs. Since recurrence has occurred after re-challenge, avoid use of high dose intravenous methylprednisolone in patients with a history of toxic hepatitis caused by methylprednisolone.

Vaccination

Administration of live or live, attenuated vaccines is contraindicated in patients receiving immunosuppressive doses of corticosteroids. Killed or inactivated vaccines may be administered. However, the response to such vaccines can not be predicted.Immunization procedures may be undertaken in patients receiving corticosteroids as replacement therapy, e.g., for Addison’s disease.

Neurologic

Reports of severe medical events have been associated with the intrathecal route of administration (see ADVERSE REACTIONS, Gastrointestinaland Neurologic/Psychiatric).

Ophthalmic

Use of corticosteroids may produce posterior subcapsular cataracts, glaucoma with possible damage to the optic nerves, and may enhance the establishment of secondary ocular infections due to bacteria, fungi, or viruses. The use of oral corticosteroids is not recommended in the treatment of optic neuritis and may lead to an increase in the risk of new episodes. Corticosteroids should be used cautiously in patients with ocular herpes simplex because of corneal perforation. Corticosteroids should not be used in active ocular herpes simplex.

Kaposi’s sarcoma has been reported to occur in patients receiving corticosteroid therapy, most often for chronic conditions. Discontinuation of corticosteroids may result in clinical improvement of Kaposi’s sarcoma.

PRECAUTIONS

General

This product, like many other steroid formulations, is sensitive to heat. Therefore, it should not be autoclaved when it is desirable to sterilize the exterior of the vial.

The lowest possible dose of corticosteroid should be used to control the condition under treatment. When reduction in dosage is possible, the reduction should be gradual.

Since complications of treatment with glucocorticoids are dependent on the size of the dose and the duration of treatment, a risk/benefit decision must be made in each individual case as to dose and duration of treatment and as to whether daily or intermittent therapy should be used.

Cardio-renal

Caution is required in patients with systemic sclerosis because an increased incidence of scleroderma renal crisis has been observed with corticosteroids, including methylprednisolone.

As sodium retention with resultant edema and potassium loss may occur in patients receiving corticosteroids, these agents should be used with caution in patients with congestive heart failure, hypertension, or renal insufficiency.

Endocrine

Drug-induced secondary adrenocortical insufficiency may be minimized by gradual reduction of dosage. This type of relative insufficiency may persist for months after discontinuation of therapy; therefore, in any situation of stress occurring during that period, hormone therapy should be reinstituted.

Metabolic clearance of corticosteroids is decreased in hypothyroid patients and increased in hyperthyroid patients. Changes in thyroid status of the patient may necessitate adjustment in dosage.

Gastrointestinal

Steroids should be used with caution in active or latent peptic ulcers, diverticulitis, fresh intestinal anastomoses, and nonspecific ulcerative colitis, since they may increase the risk of a perforation. Signs of peritoneal irritation following gastrointestinal perforation in patients receiving corticosteroids may be minimal or absent.

There is an enhanced effect due to decreased metabolism of corticosteroids in patients with cirrhosis.

Musculoskeletal

Corticosteroids decrease bone formation and increase bone resorption both through their effect on calcium regulation (i.e., decreasing absorption and increasing excretion) and inhibition of osteoblast function. This, together with a decrease in the protein matrix of the bone secondary to an increase in protein catabolism, and reduced sex hormone production, may lead to inhibition of bone growth in pediatric patients and the development of osteoporosis at any age. Special consideration should be given to patients at increased risk of osteoporosis (i.e., postmenopausal women) before initiating corticosteroid therapy.

Local injection of a steroid into a previously infected site is not usually recommended.

Neurologic-psychiatric

Although controlled clinical trials have shown corticosteroids to be effective in speeding the resolution of acute exacerbations of multiple sclerosis, they do not show that corticosteroids affect the ultimate outcome or natural history of the disease. The studies do show that relatively high doses of corticosteroids are necessary to demonstrate a significant effect (see DOSAGE AND ADMINISTRATION).

An acute myopathy has been observed with the use of high doses of corticosteroids, most often occurring in patients with disorders of neuromuscular transmission (e.g., myasthenia gravis), or in patients receiving concomitant therapy with neuromuscular blocking drugs (e.g., pancuronium). This acute myopathy is generalized, may involve ocular and respiratory muscles, and may result in quadriparesis. Elevations of creatine kinase may occur. Clinical improvement or recovery after stopping corticosteroids may require weeks to years.

Psychic derangements may appear when corticosteroids are used, ranging from euphoria, insomnia, mood swings, personality changes, and severe depression, to frank psychotic manifestations. Also, existing emotional instability or psychotic tendencies may be aggravated by corticosteroids.

Ophthalmic

Intraocular pressure may become elevated in some individuals. If steroid therapy is continued for more than 6 weeks, intraocular pressure should be monitored.

Tumor Lysis Syndrome

In post marketing experience, tumor lysis syndrome (TLS) has been reported in patients with malignancies, including hematological malignancies and solid tumors, following the use of systemic corticosteroids alone or in combination with other chemotherapeutic agents. Patients at high risk of TLS, such as patients with tumors that have a high proliferative rate, high tumor burden and high sensitivity to cytotoxic agents, should be monitored closely and appropriate precautions should be taken.

Information for Patients

Patients should be warned not to discontinue the use of corticosteroids abruptly or without medical supervision, to advise any medical attendants that they are taking corticosteroids, and to seek medical advice at once should they develop fever or other signs of infection.

Persons who are on corticosteroids should be warned to avoid exposure to chicken pox or measles. Patients should also be advised that if they are exposed, medical advice should be sought without delay.

Repackaged By / Distributed By: RemedyRepack Inc.

625 Kolter Drive, Indiana, PA 15701

(724) 465-8762

Drug Interactions

Aminoglutethimide: Aminoglutethimide may lead to a loss of corticosteroid-induced adrenal suppression.

Amphotericin B injection and potassium-depleting agents:When corticosteroids are administered concomitantly with potassium-depleting agents (i.e., amphotericin B, diuretics), patients should be observed closely for development of hypokalemia. There have been cases reported in which concomitant use of amphotericin B and hydrocortisone was followed by cardiac enlargement and congestive heart failure.

Antibiotics: Macrolide antibiotics have been reported to cause a significant decrease in corticosteroid clearance (see Drug Interactions, Hepatic Enzyme Inhibitors).

Anticholinesterases: Concomitant use of anticholinesterase agents and corticosteroids may produce severe weakness in patients with myasthenia gravis. If possible, anticholinesterase agents should be withdrawn at least 24 hours before initiating corticosteroid therapy.

Anticoagulants, oral: Coadministration of corticosteroids and warfarin usually results in inhibition of response to warfarin, although there have been some conflicting reports. Therefore, coagulation indices should be monitored frequently to maintain the desired anticoagulant effect.

Antidiabetics: Because corticosteroids may increase blood glucose concentrations, dosage adjustments of antidiabetic agents may be required.

Antitubercular drugs: Serum concentrations of isoniazid may be decreased.

Cholestyramine: Cholestyramine may increase the clearance of corticosteroids.

Cyclosporine: Increased activity of both cyclosporine and corticosteroids may occur when the two are used concurrently. Convulsions have been reported with this concurrent use.

Digitalis glycosides: Patients on digitalis glycosides may be at increased risk of arrhythmias due to hypokalemia.

Estrogens, including oral contraceptives: Estrogens may decrease the hepatic metabolism of certain corticosteroids, thereby increasing their effect.

Hepatic Enzyme Inducers (e.g., barbiturates, phenytoin, carbamazepine, rifampin): Drugs which induce cytochrome P450 3A4 enzyme activity may enhance the metabolism of corticosteroids and require that the dosage of the corticosteroid be increased.

Hepatic Enzyme Inhibitors (e.g., ketoconazole, macrolide antibiotics such as erythromycin and troleandomycin): Drugs which inhibit cytochrome P450 3A4 have the potential to result in increased plasma concentrations of corticosteroids.

Ketoconazole: Ketoconazole has been reported to significantly decrease the metabolism of certain corticosteroids by up to 60%, leading to an increased risk of corticosteroid side effects.

Nonsteroidal anti-inflammatory agents (NSAIDs): Concomitant use of aspirin (or other nonsteroidal anti-inflammatory agents) and corticosteroids increases the risk of gastrointestinal side effects. Aspirin should be used cautiously in conjunction with corticosteroids in hypoprothrombinemia. The clearance of salicylates may be increased with concurrent use of corticosteroids.

Skin tests: Corticosteroids may suppress reactions to skin tests.

Vaccines: Patients on prolonged corticosteroid therapy may exhibit a diminished response to toxoids and live or inactivated vaccines due to inhibition of antibody response. Corticosteroids may also potentiate the replication of some organisms contained in live attenuated vaccines. Routine administration of vaccines or toxoids should be deferred until corticosteroid therapy is discontinued if possible (see WARNINGS, Immunosuppression and Increased Risk of Infection, Vaccination).

Carcinogenesis, Mutagenesis, Impairment of Fertility

No adequate studies have been conducted in animals to determine whether corticosteroids have a potential for carcinogenesis or mutagenesis.

Steroids may increase or decrease motility and number of spermatozoa in some patients.

Corticosteroids have been shown to impair fertility in male rats.

Pregnancy:

Teratogenic Effects

Corticosteroids have been shown to be teratogenic in many species when given in doses equivalent to the human dose. Animal studies in which corticosteroids have been given to pregnant mice, rats, and rabbits have yielded an increased incidence of cleft palate in the offspring. There are no adequate and well-controlled studies in pregnant women. Corticosteroids should be used during pregnancy only if the potential benefit justifies the potential risk to the fetus. Infants born to mothers who have received corticosteroids during pregnancy should be carefully observed for signs of hypoadrenalism.

This product contains benzyl alcohol as a preservative.

Benzyl alcohol can cross the placenta. See PRECAUTIONS: Pediatric use.

Nursing Mothers

Systemically administered corticosteroids appear in human milk and could suppress growth, interfere with endogenous corticosteroid production, or cause other untoward effects. Because of the potential for serious adverse reactions in nursing infants from corticosteroids, a decision should be made whether to continue nursing, or discontinue the drug, taking into account the importance of the drug to the mother.

Pediatric Use

Some formulations of this product contain benzyl alcohol as a preservative (see DESCRIPTION). Carefully examine vials to determine formulation that is being used.

Benzyl alcohol, a component of this product, has been associated with serious adverse events and death, particularly in pediatric patients. The "gasping syndrome" (characterized by central nervous system depression, metabolic acidosis, gasping respirations, and high levels of benzyl alcohol and its metabolites found in the blood and urine) has been associated with benzyl alcohol dosages >99 mg/kg/day in neonates and low-birth-weight neonates. Additional symptoms may include gradual neurological deterioration, seizures, intracranial hemorrhage, hematologic abnormalities, skin breakdown, hepatic and renal failure, hypotension, bradycardia, and cardiovascular collapse. Although normal therapeutic doses of this product ordinarily delivers amounts of benzyl alcohol that are substantially lower than those reported in association with the "gasping syndrome", the minimum amount of benzyl alcohol at which toxicity may occur is not known. The risk of benzyl alcohol toxicity depends on the quantity administered and the hepatic capacity to detoxify the chemical. Premature and low-birth-weight infants, as well as patients receiving high dosages, may be more likely to develop toxicity. Practitioners administering this and other medications containing benzyl alcohol should consider the combined daily metabolic load of benzyl alcohol from all sources.

The efficacy and safety of corticosteroids in the pediatric population are based on the well-established course of effect of corticosteroids which is similar in pediatric and adult populations. Published studies provide evidence of efficacy and safety in pediatric patients for the treatment of nephrotic syndrome (>2 years of age), and aggressive lymphomas and leukemias (>1 month of age). Other indications for pediatric use of corticosteroids, e.g., severe asthma and wheezing, are based on adequate and well-controlled trials conducted in adults, on the premises that the course of the diseases and their pathophysiology are considered to be substantially similar in both populations.

The adverse effects of corticosteroids in pediatric patients are similar to those in adults (see ADVERSE REACTIONS). Like adults, pediatric patients should be carefully observed with frequent measurements of blood pressure, weight, height, intraocular pressure, and clinical evaluation for the presence of infection, psychosocial disturbances, thromboembolism, peptic ulcers, cataracts, and osteoporosis. Pediatric patients who are treated with corticosteroids by any route, including systemically administered corticosteroids, may experience a decrease in their growth velocity. This negative impact of corticosteroids on growth has been observed at low systemic doses and in the absence of laboratory evidence of HPA axis suppression (i.e., cosyntropin stimulation and basal cortisol plasma levels). Growth velocity may therefore be a more sensitive indicator of systemic corticosteroid exposure in pediatric patients than some commonly used tests of HPA axis function. The linear growth of pediatric patients treated with corticosteroids should be monitored, and the potential growth effects of prolonged treatment should be weighed against clinical benefits obtained and the availability of treatment alternatives. In order to minimize the potential growth effects of corticosteroids, pediatric patients should be titrated to the lowest effective dose.

Hypertrophic cardiomyopathy may develop after administration of methylprednisolone to prematurely born infants, therefore appropriate diagnostic evaluation and monitoring of cardiac function and structure should be performed.

Geriatric Use

Clinical studies did not include sufficient numbers of subjects aged 65 and over to determine whether they respond differently from younger subjects. Other reported clinical experience has not identified differences in responses between the elderly and younger patients. In general, dose selection for an elderly patient should be cautious, usually starting at the low end of the dosing range, reflecting the greater frequency of decreased hepatic, renal, or cardiac function, and of concomitant disease or other drug therapy.

ADVERSE REACTIONS

The following adverse reactions have been reported with SOLU-MEDROL or other corticosteroids:

Allergic reactions:Allergic or hypersensitivity reactions, anaphylactoid reaction, anaphylaxis, angioedema.

Blood and lymphatic system disorders:Leukocytosis.

Cardiovascular:Bradycardia, cardiac arrest, cardiac arrhythmias, cardiac enlargement, circulatory collapse, congestive heart failure, fat embolism, hypertension, hypertrophic cardiomyopathy in premature infants, myocardial rupture following recent myocardial infarction (see WARNINGS), pulmonary edema, syncope, tachycardia, thromboembolism, thrombophlebitis, vasculitis.

Dermatologic:Acne, allergic dermatitis, burning or tingling (especially in the perineal area after intravenous injection), cutaneous and subcutaneous atrophy, dry scaly skin, ecchymoses and petechiae, edema, erythema, hyperpigmentation, hypopigmentation, impaired wound healing, increased sweating, rash, sterile abscess, striae, suppressed reactions to skin tests, thin fragile skin, thinning scalp hair, urticaria.

Endocrine:Decreased carbohydrate and glucose tolerance, development of cushingoid state, glycosuria, hirsutism, hypertrichosis, increased requirements for insulin or oral hypoglycemic agents in diabetes, manifestations of latent diabetes mellitus, menstrual irregularities, secondary adrenocortical and pituitary unresponsiveness (particularly in times of stress, as in trauma, surgery, or illness), suppression of growth in pediatric patients.

Fluid and electrolyte disturbances:Congestive heart failure in susceptible patients, fluid retention, hypokalemic alkalosis, potassium loss, sodium retention.

Gastrointestinal:Abdominal distention, bowel/bladder dysfunction (after intrathecal administration), elevation in serum liver enzyme levels (usually reversible upon discontinuation), hepatomegaly, increased appetite, nausea, pancreatitis, peptic ulcer with possible perforation and hemorrhage, perforation of the small and large intestine (particularly in patients with inflammatory bowel disease), ulcerative esophagitis.

Hepatobiliary:Hepatitis (see WARNINGS, Drug-Induced Liver Injury).

Metabolic:Negative nitrogen balance due to protein catabolism.

Musculoskeletal:Aseptic necrosis of femoral and humeral heads, Charcot-like arthropathy, loss of muscle mass, muscle weakness, osteoporosis, pathologic fracture of long bones, postinjection flare (following intra-articular use), steroid myopathy, tendon rupture, vertebral compression fractures.

Neurologic/Psychiatric:Convulsions, depression, emotional instability, euphoria, headache, increased intracranial pressure with papilledema (pseudotumor cerebri) usually following discontinuation of treatment, insomnia, mood swings, neuritis, neuropathy, paresthesia, personality changes, psychic disorders, vertigo. Arachnoiditis, meningitis, paraparesis/paraplegia, and sensory disturbances have occurred after intrathecal administration (see WARNINGS, Neurologic).

Ophthalmic:Exophthalmos, glaucoma, increased intraocular pressure, posterior subcapsular cataracts, rare instances of blindness associated with periocular injections.

Vascular:Flushing.

Other:Abnormal fat deposits, decreased resistance to infection, hiccups, increased or decreased motility and number of spermatozoa, injection site infections following non-sterile administration (see WARNINGS), malaise, moon face, weight gain.

OVERDOSAGE

Treatment of acute overdosage is by supportive and symptomatic therapy. For chronic overdosage in the face of severe disease requiring continuous steroid therapy, the dosage of the corticosteroid may be reduced only temporarily, or alternate day treatment may be introduced.

DOSAGE AND ADMINISTRATION

NOTE: Some of the SOLU-MEDROL formulations contain benzyl alcohol (see DESCRIPTION, WARNINGSand PRECAUTIONS, Pediatric Use)

Because of possible physical incompatibilities, SOLU-MEDROL should not be diluted or mixed with other solutions.

Use only the accompanying diluent or Bacteriostatic Water For Injection with Benzyl Alcohol when reconstituting SOLU-MEDROL (see DESCRIPTION).

Parenteral drug products should be inspected visually for particulate matter and discoloration prior to administration, whenever solution and container permit.

This preparation may be administered by intravenous injection, by intravenous infusion, or by intramuscular injection, the preferred method for initial emergency use being intravenous injection. Following the initial emergency period, consideration should be given to employing a longer acting injectable preparation or an oral preparation.

There are reports of cardiac arrhythmias and/or cardiac arrest following the rapid administration of large intravenous doses of SOLU-MEDROL (greater than 0.5 gram administered over a period of less than 10 minutes). Bradycardia has been reported during or after the administration of large doses of methylprednisolone sodium succinate, and may be unrelated to the speed or duration of infusion. When high dose therapy is desired, the recommended dose of SOLU-MEDROL Sterile Powder is 30 mg/kg administered intravenously over at least 30 minutes. This dose may be repeated every 4 to 6 hours for 48 hours.

In general, high dose corticosteroid therapy should be continued only until the patient's condition has stabilized; usually not beyond 48 to 72 hours.

In other indications, initial dosage will vary from 10 to 40 mg of methylprednisolone depending on the specific disease entity being treated. However, in certain overwhelming, acute, life-threatening situations, administrations in dosages exceeding the usual dosages may be justified and may be in multiples of the oral dosages.

It Should Be Emphasized that Dosage Requirements are Variable and Must Be Individualized on the Basis of the Disease Under Treatment and the Response of the Patient.After a favorable response is noted, the proper maintenance dosage should be determined by decreasing the initial drug dosage in small decrements at appropriate time intervals until the lowest dosage which will maintain an adequate clinical response is reached. Situations which may make dosage adjustments necessary are changes in clinical status secondary to remissions or exacerbations in the disease process, the patient's individual drug responsiveness, and the effect of patient exposure to stressful situations not directly related to the disease entity under treatment. In this latter situation, it may be necessary to increase the dosage of the corticosteroid for a period of time consistent with the patient's condition. If after long-term therapy the drug is to be stopped, it is recommended that it be withdrawn gradually rather than abruptly.

SOLU-MEDROL may be administered by intravenous or intramuscular injection or by intravenous infusion, the preferred method for initial emergency use being intravenous injection. To administer by intravenous (or intramuscular) injection, prepare solution as directed. The desired dose may be administered intravenously over a period of several minutes. If desired, the medication may be administered in diluted solutions by adding Water for Injection or other suitable diluent (see below) to the Act-O-Vialand withdrawing the indicated dose.

To prepare solutions for intravenous infusion, first prepare the solution for injection as directed. This solution may then be added to indicated amounts of 5% dextrose in water, isotonic saline solution, or 5% dextrose in isotonic saline solution. From a microbiological point of view, unless the method of opening/reconstitution/dilution precludes the risk of microbial contamination, the product should be used immediately. If not used immediately, in-use storage times and conditions are the responsibility of the user. Chemical and physical stability of the further diluted product has been demonstrated within 4 hours of preparation if stored below 25°C or within 24 hours of preparation if stored at 2°C to 8°C.

In pediatric patients, the initial dose of methylprednisolone may vary depending on the specific disease entity being treated. The range of initial doses is 0.11 to 1.6 mg/kg/day in three or four divided doses (3.2 to 48 mg/m^2bsa/day).

The National Heart, Lung, and Blood Institute (NHLBI) recommended dosing for systemic prednisone, prednisolone, or methylprednisolonein pediatric patients whose asthma is uncontrolled by inhaled corticosteroids and long-acting bronchodilators is 1–2 mg/kg/day in single or divided doses. It is further recommended that short course, or "burst" therapy, be continued until the patient achieves a peak expiratory flow rate of 80% of his or her personal best or until symptoms resolve. This usually requires 3 to 10 days of treatment, although it can take longer. There is no evidence that tapering the dose after improvement will prevent a relapse.

Dosage may be reduced for infants and children but should be governed more by the severity of the condition and response of the patient than by age or size. It should not be less than 0.5 mg per kg every 24 hours.

Dosage must be decreased or discontinued gradually when the drug has been administered for more than a few days. If a period of spontaneous remission occurs in a chronic condition, treatment should be discontinued. Routine laboratory studies, such as urinalysis, two-hour postprandial blood sugar, determination of blood pressure and body weight, and a chest X-ray should be made at regular intervals during prolonged therapy. Upper GI X-rays are desirable in patients with an ulcer history or significant dyspepsia.

In treatment of acute exacerbations of multiple sclerosis, daily doses of 160 mg of methylprednisolone for a week followed by 64 mg every other day for 1 month have been shown to be effective (see PRECAUTIONS, Neurologic-psychiatric).

For the purpose of comparison, the following is the equivalent milligram dosage of the various glucocorticoids:

Cortisone, 25 | Triamcinolone, 4
Hydrocortisone, 20 | Paramethasone, 2
Prednisolone, 5 | Betamethasone, 0.75
Prednisone, 5 | Dexamethasone, 0.75
Methylprednisolone, 4

These dose relationships apply only to oral or intravenous administration of these compounds. When these substances or their derivatives are injected intramuscularly or into joint spaces, their relative properties may be greatly altered.

DIRECTIONS FOR USING THE ACT-O-VIAL SYSTEM

1. Press down on plastic activator to force diluent into the lower compartment.
2. Gently agitate to effect solution.
3. Remove plastic tab covering center of stopper.
4. Sterilize top of stopper with a suitable germicide.
5. Insert needle squarely through centerof stopper until tip is just visible. Invert vial and withdraw dose.

STORAGE CONDITIONS

Protect from light.

Store unreconstituted product at controlled room temperature 20° to 25°C (68° to 77°F) [see USP].

Store reconstituted solution (not further diluted) at controlled room temperature 20° to 25°C (68° to 77°F) [see USP], and use it within 48 hours.

See section DOSAGE AND ADMINISTRATION, for storage of further diluted solution.

HOW SUPPLIED

SOLU-MEDROL Sterile Powder preservative-free is available in the following packages

125 mg Act-O-Vial System (Single-Dose Vial)

25 × 2 mL

NDC: 70518-2023-00

NDC: 70518-2023-01

PACKAGING: 25 in 1 CARTON

PACKAGING: 2 mL in 1 VIAL, TYPE 0

Repackaged and Distributed By:

Remedy Repack, Inc.

625 Kolter Dr. Suite #4 Indiana, PA 1-724-465-8762

Relabeled and Distributed By:

Remedy Repack, Inc.

625 Kolter Dr. Suite #4 Indiana, PA 1-724-465-8762

PACKAGE LABEL

DRUG: SOLU-MEDROL

GENERIC: methylprednisolone sodium succinate

DOSAGE: INJECTION, POWDER, FOR SOLUTION

ADMINSTRATION: INTRAVENOUS

NDC: 70518-2023-0

NDC: 70518-2023-1

PACKAGING: 2 mL in 1 VIAL

OUTER PACKAGING: 25 in 1 CARTON

ACTIVE INGREDIENT(S):

- METHYLPREDNISOLONE SODIUM SUCCINATE 125mg in 2mL

INACTIVE INGREDIENT(S):

- SODIUM PHOSPHATE, MONOBASIC, ANHYDROUS
- SODIUM PHOSPHATE, DIBASIC, UNSPECIFIED FORM